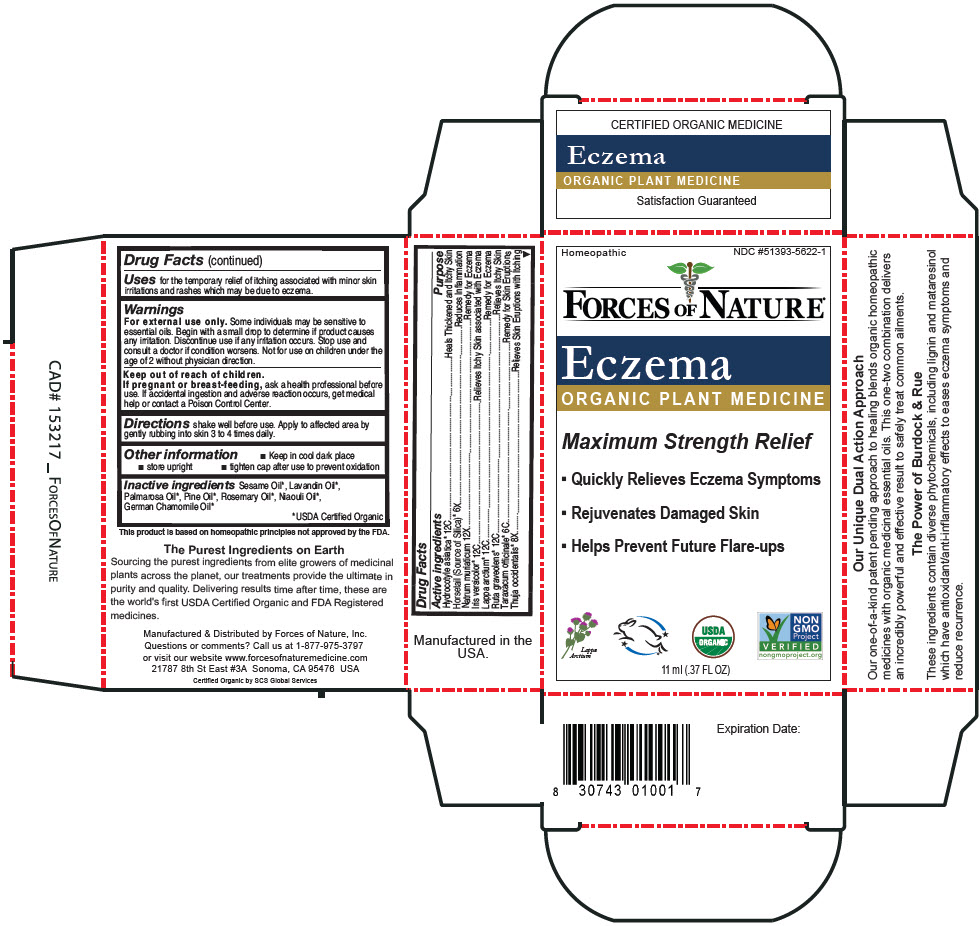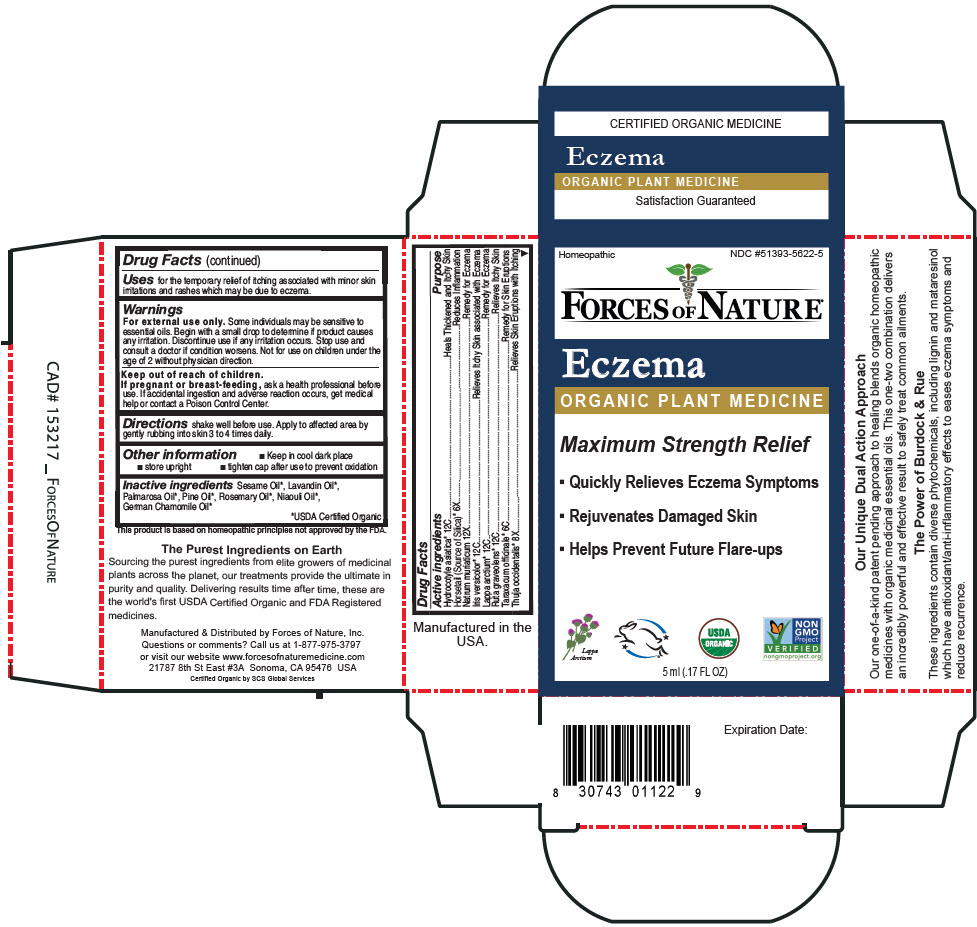 DRUG LABEL: Eczema Control
NDC: 51393-5622 | Form: SOLUTION/ DROPS
Manufacturer: Forces of Nature
Category: homeopathic | Type: HUMAN OTC DRUG LABEL
Date: 20250424

ACTIVE INGREDIENTS: Centella Asiatica Whole 12 [hp_C]/100 mL; Iris Versicolor Root 12 [hp_C]/100 mL; Arctium Lappa Root 12 [hp_C]/100 mL; Sodium Chloride 12 [hp_X]/100 mL; Ruta Graveolens Flowering Top 12 [hp_C]/100 mL; Silicon Dioxide 6 [hp_X]/100 mL; Taraxacum Officinale 6 [hp_C]/100 mL; Thuja Occidentalis Root 8 [hp_X]/100 mL
INACTIVE INGREDIENTS: Pine Needle Oil (Pinus Sylvestris); Rosemary Oil; Lavandin Oil; Niaouli Oil; Palmarosa Oil; Matricaria Chamomilla Flowering Top Oil; Sesame Oil

ECZEMA CONTROL

Drug Facts

ACTIVE INGREDIENT

Active ingredients | Purpose
Hydrocotyle asiatica [USDA Certified Organic] 12C | Heals Thickened and Itchy Skin
Horsetail (Source of Silica) 6X | Reduces Inflammation
Natrum muriaticum 12X | Remedy for Eczema
Iris versicolor 12C | Relieves Itchy Skin associated with Eczema
Lappa arctium 12C | Remedy for Eczema
Ruta graveolens 12C | Relieves Itchy Skin
Taraxacum officinale 6C | Remedy for Skin Eruptions
Thuja occidentalis 8X | Relieves Skin Eruptions with Itching

Uses

for the temporary relief of itching associated with minor skin irritations and rashes which may be due to eczema.

Warnings

For external use only. Some individuals may be sensitive to essential oils. Begin with a small drop to determine if product causes any irritation. Discontinue use if any irritation occurs. Stop use and consult a doctor if condition worsens. Not for use on children under the age of 2 without physician direction.

Keep out of reach of children.

PREGNANCY OR BREAST FEEDING

If pregnant or breast-feeding, ask a health professional before use. If accidental ingestion and adverse reaction occurs, get medical help or contact a Poison Control Center.

Directions

shake well before use. Apply to affected area by gently rubbing into skin 3 to 4 times daily.

Other information

- Keep in cool dark place
- store upright
- tighten cap after use to prevent oxidation

Inactive ingredients

Sesame Oil, Lavandin Oil, Palmarosa Oil, Pine Oil, Rosemary Oil, Niaouli Oil, German Chamomile Oil

Questions or comments?

Call us at 1-877-975-3797 or visit our website www.forcesofnaturemedicine.com

Manufactured & Distributed by Forces of Nature, Inc.
21787 8th St East #3A Sonoma, CA 95476 USA

PRINCIPAL DISPLAY PANEL - 11 ml Bottle Carton

Homeopathic
NDC #51393-5622-1

FORCES OF NATURE®

Eczema
ORGANIC PLANT MEDICINE

Maximum Strength Relief

- Quickly Relieves Eczema Symptoms
- Rejuvenates Damaged Skin
- Helps Prevent Future Flare-ups

11 ml (.37 FL OZ)

PRINCIPAL DISPLAY PANEL - 5 ml Bottle Carton

Homeopathic
NDC #51393-5622-5

FORCES OF NATURE®

Eczema
ORGANIC PLANT MEDICINE

Maximum Strength Relief

- Quickly Relieves Eczema Symptoms
- Rejuvenates Damaged Skin
- Helps Prevent Future Flare-ups

5 ml (.17 FL OZ)